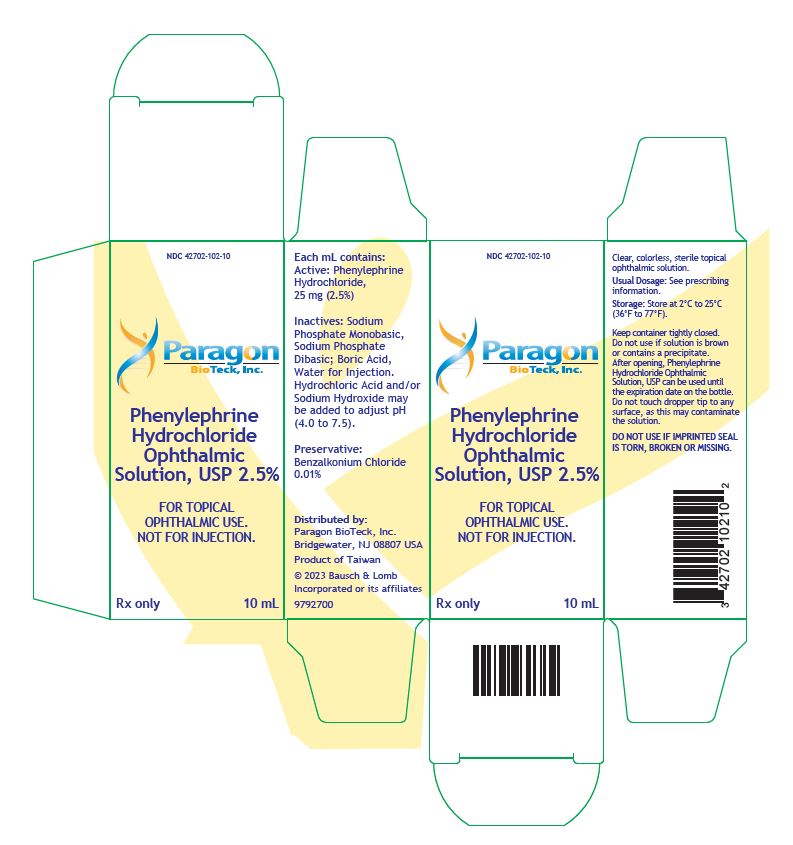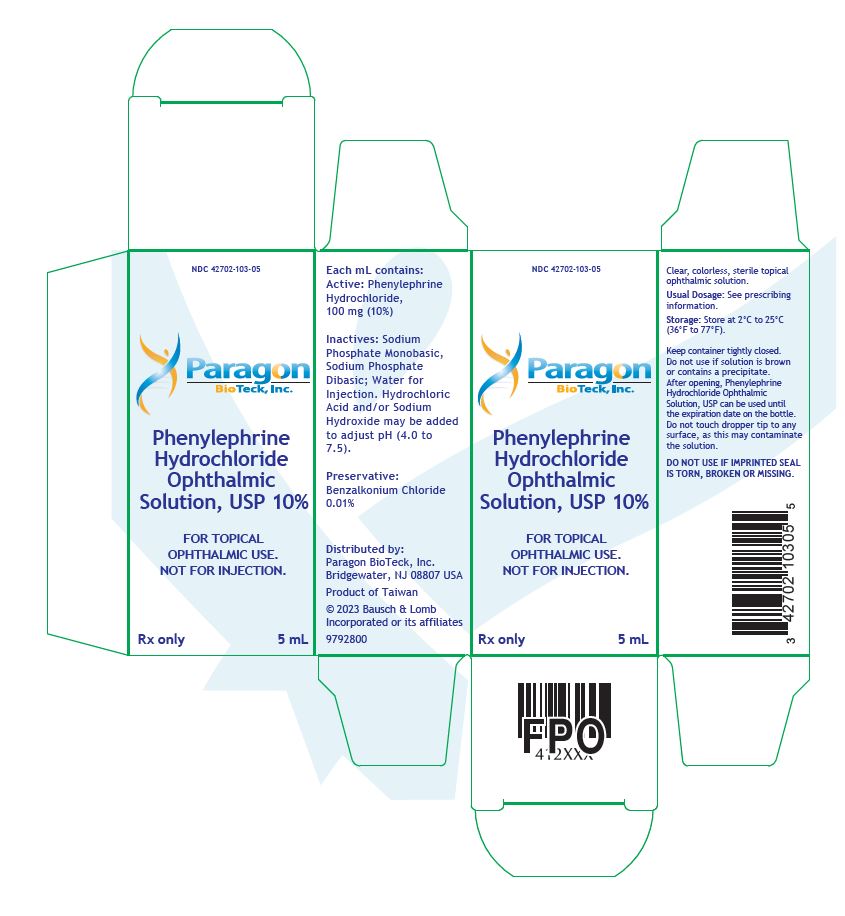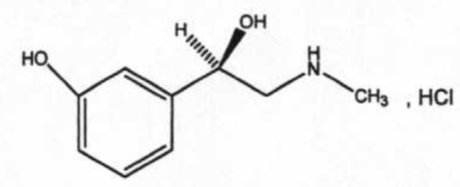 DRUG LABEL: Phenylephrine Hydrochloride
NDC: 42702-103 | Form: SOLUTION/ DROPS
Manufacturer: Paragon BioTeck, Inc.
Category: prescription | Type: HUMAN PRESCRIPTION DRUG LABEL
Date: 20230629

ACTIVE INGREDIENTS: PHENYLEPHRINE HYDROCHLORIDE 100 mg/1 mL
INACTIVE INGREDIENTS: HYDROCHLORIC ACID; SODIUM HYDROXIDE; BORIC ACID; WATER; SODIUM PHOSPHATE, DIBASIC, UNSPECIFIED FORM; SODIUM PHOSPHATE, MONOBASIC, UNSPECIFIED FORM

HIGHLIGHTS OF PRESCRIBING INFORMATION

These highlights do not include all the information needed to use PHENYLEPHRINE HYDROCHLORIDE OPHTHALMIC SOLUTION, USP 2.5% and 10% safely and effectively. See full prescribing information for PHENYLEPHRINE HYDROCHLORIDE OPHTHALMIC SOLUTION, USP 2.5% and 10%.
PHENYLEPHRINE HYDROCHLORIDE OPHTHALMIC SOLUTION, USP 2.5% and 10%, for topical ophthalmic use
Initial U.S. Approval: 1939

1 INDICATIONS AND USAGE

Phenylephrine Hydrochloride Ophthalmic Solution, USP 2.5% and 10% is an alpha-1 adrenergic receptor agonist indicated to dilate the pupil (1).

2 DOSAGE AND ADMINISTRATION

- For patients 1 year of age and older, apply one drop of Phenylephrine Hydrochloride Ophthalmic Solution, USP 2.5% or 10% at 3 to 5 minute intervals up to a maximum of 3 drops per eye (2.1).
- In pediatric patients less than 1 year of age, one drop of Phenylephrine Hydrochloride Ophthalmic Solution, USP 2.5% should be instilled at 3 to 5 minute intervals up to a maximum of 3 drops per eye (2.2).

3 DOSAGE FORMS AND STRENGTHS

2.5% and 10% sterile ophthalmic solutions (3).

4 CONTRAINDICATIONS

- Phenylephrine Hydrochloride Ophthalmic Solution, USP 10% is contraindicated in patients with hypertension, or thyrotoxicosis. Phenylephrine Hydrochloride Ophthalmic Solution, USP 2.5% should be used in these patients (4.1).
- Phenylephrine Hydrochloride Ophthalmic Solution, USP 10% is contraindicated in pediatric patients less than 1 year of age due to the increased risk of systemic toxicity. Phenylephrine Hydrochloride Ophthalmic Solution, USP 2.5% should be used in these patients (4.2).

5 WARNINGS AND PRECAUTIONS

- Not for injection. Phenylephrine Hydrochloride Ophthalmic Solution, USP is indicated for topical ophthalmic use (5.1).
- Reports of serious cardiovascular reactions, some fatal, with Phenylephrine Hydrochloride Ophthalmic Solution, USP 10% solution. Monitor blood pressure in patients with cardiovascular disease (5.2).
- Significant elevations in blood pressure have been reported. Caution in pediatric patients less than 5 years of age, and in patients with elevated blood pressure (5.3).
- Rebound miosis has been reported one day after instillation (5.4).

6 ADVERSE REACTIONS

- Ocular adverse reactions include eye pain and stinging on instillation, temporary blurred vision, and photophobia (6.1).
- Cardiovascular adverse reactions include increase in blood pressure, syncope, myocardial infarction, tachycardia, arrhythmia and subarachnoid hemorrhage (6.2).

To report SUSPECTED ADVERSE REACTIONS, contact Paragon BioTeck, Inc. at 1-800-553-5340 or FDA at 1-800-FDA-1088 or www.fda.gov/medwatch.

7 DRUG INTERACTIONS

- May exaggerate the adrenergic pressor response in patients taking atropine-like drugs (7.1).
- May potentiate the cardiovascular depressant effects of potent inhalation anesthetic agents (7.1).

FULL PRESCRIBING INFORMATION

1 INDICATIONS AND USAGE

Phenylephrine Hydrochloride Ophthalmic Solution, USP 2.5% and 10% is indicated to dilate the pupil.

2 DOSAGE AND ADMINISTRATION

2.1 General Dosing Recommendations

For patients 1 year of age or greater, apply one drop of either Phenylephrine Hydrochloride Ophthalmic Solution, USP 2.5% or 10% every 3 to 5 minutes to the conjunctival fornix as required up to a maximum of 3 drops. If necessary, this dose may be repeated.

In order to obtain a greater degree of mydriasis, Phenylephrine Hydrochloride Ophthalmic Solution, USP 10% may be needed.

2.2 Pediatric Patients Less Than 1 Year of Age

In pediatric patients less than 1 year of age, one drop of Phenylephrine Hydrochloride Ophthalmic Solution, USP 2.5% should be instilled at 3 to 5 minute intervals up to a maximum of 3 drops per eye.

3 DOSAGE FORMS AND STRENGTHS

Phenylephrine Hydrochloride Ophthalmic Solution, USP 2.5% is a clear, colorless, sterile topical ophthalmic solution containing phenylephrine hydrochloride 2.5%.

Phenylephrine Hydrochloride Ophthalmic Solution, USP 10% is a clear, colorless, sterile topical ophthalmic solution containing phenylephrine hydrochloride 10%.

4 CONTRAINDICATIONS

4.1 Cardiac and Endocrine Disease

Phenylephrine Hydrochloride Ophthalmic Solution, USP 10% is contraindicated in patients with hypertension, or thyrotoxicosis. Phenylephrine Hydrochloride Ophthalmic Solution, USP 2.5% should be used in these patients.

4.2 Pediatric Patients Less Than 1 Year of Age

Phenylephrine Hydrochloride Ophthalmic Solution, USP 10% is contraindicated in pediatric patients less than 1 year of age due to the increased risk of systemic toxicity. Phenylephrine Hydrochloride Ophthalmic Solution, USP 2.5% should be used in these patients [See Dosage and Administration (2.2)].

5 WARNINGS AND PRECAUTIONS

5.1 Topical Ophthalmic Use

Phenylephrine Hydrochloride Ophthalmic Solution, USP 2.5% and 10% is not indicated for injection.

5.2 Cardiovascular Reactions

There have been reports of serious cardiovascular reactions, including ventricular arrhythmias and myocardial infarctions, in patients using phenylephrine 10%. These episodes, some fatal, have usually occurred in patients with pre-existing cardiovascular diseases. Phenylephrine Hydrochloride Ophthalmic Solution, USP 2.5% should be used in these patients.

5.3 Elevation in Blood Pressure

A significant elevation in blood pressure is not common but has been reported following conjunctival instillation of recommended doses of phenylephrine 10%. The risk is less with phenylephrine 2.5%. Caution should be exercised with the use of phenylephrine 10% in pediatric patients less than 5 years of age and patients with hyperthyroidism or cardiovascular disease. The post-treatment blood pressure of patients with cardiac and endocrine diseases and any patients who develop symptoms should be carefully monitored.

5.4 Rebound Miosis

Rebound miosis has been reported one day after receiving phenylephrine ophthalmic solution, and re instillation of the drug produced a lesser mydriatic effect.

6 ADVERSE REACTIONS

The following serious adverse reactions are described below and elsewhere in the labeling:

- Cardiac Disease [See Warnings and Precautions (5.2)].
- Elevation in Blood Pressure [See Warnings and Precautions (5.3)].

The following adverse reactions have been identified following use of phenylephrine hydrochloride ophthalmic solution. Because these reactions are reported voluntarily from a population of uncertain size, it is not always possible to reliably estimate their frequency or establish a causal relationship to drug exposure.

6.1 Ocular Adverse Reactions

Eye pain and stinging on instillation, temporary blurred vision and photophobia, and conjunctival sensitization may occur.

6.2 Systemic Adverse Reactions

A marked increase in blood pressure has been reported particularly, but not limited to, low weight premature neonates, infants and hypertensive patients.

Cardiovascular reactions which have occurred primarily in hypertensive patients following topical ocular use of phenylephrine hydrochloride ophthalmic solution 10% include marked increase in blood pressure, syncope, myocardial infarction, tachycardia, arrhythmia and subarachnoid hemorrhage [See Warnings and Precautions (5.2and 5.3)].

7 DRUG INTERACTIONS

7.1 Agents That May Exaggerate Pressor Responses

Concomitant use of phenylephrine and atropine may enhance the pressor effects and induce tachycardia in some patients. Phenylephrine may potentiate the cardiovascular depressant effects of some inhalation anesthetic agents.

8 USE IN SPECIFIC POPULATIONS

8.1 Pregnancy

Animal reproduction studies have not been conducted with topical phenylephrine. It is also not known whether phenylephrine can cause fetal harm when administered to a pregnant woman or can affect reproduction capacity. Phenylephrine Hydrochloride Ophthalmic Solution, USP 2.5% and 10% should be given to a pregnant woman only if clearly needed.

8.3 Nursing Mothers

It is not known whether this drug is excreted in human breast milk. Because many drugs are excreted in human milk, caution should be exercised when Phenylephrine Hydrochloride Ophthalmic Solution, USP 2.5% and 10% is administered to a nursing woman.

8.4 Pediatric Use

Phenylephrine Hydrochloride Ophthalmic Solution, USP 10% is contraindicated in pediatric patients less than 1 year of age. [See Contraindications (4.2)] .

8.5 Geriatric Use

No overall differences in safety and effectiveness have been observed between elderly and younger adult patients.

10 OVERDOSAGE

Overdosage of phenylephrine may cause a rapid rise in blood pressure. It may also cause headache, anxiety, nausea, and vomiting and ventricular arrhythmias. Prompt injection of a rapidly acting alpha-adrenergic blocking agent such as phentolamine has been recommended.

11 DESCRIPTION

Phenylephrine Hydrochloride Ophthalmic Solution, USP 2.5% and 10% is a sterile, clear, colorless, topical mydriatic agent for ophthalmic use. The chemical name is (R)-3-hydroxy-α-[(methylamino)methyl]benzenemethanol hydrochloride. Phenylephrine hydrochloride is represented by the following structural formula:

Phenylephrine hydrochloride has a molecular weight of 203.67 and an empirical formula of C9H13NO2-HCl.

Each mL of Phenylephrine Hydrochloride Ophthalmic Solution, 2.5% contains: ACTIVE: phenylephrine hydrochloride 25 mg (2.5%); INACTIVES: sodium phosphate monobasic, sodium phosphate dibasic; boric acid, water for injection. Hydrochloric acid and/or sodium hydroxide may be added to adjust pH (4.0-7.5). The solution has a tonicity of 500 mOsm/kg; PRESERVATIVE: benzalkonium chloride 0.01%.

Each mL of Phenylephrine Hydrochloride Ophthalmic Solution, USP 10% contains: ACTIVE: phenylephrine hydrochloride 100 mg (10%); INACTIVES: sodium phosphate monobasic, sodium phosphate dibasic; water for injection. Hydrochloric acid and/or sodium hydroxide may be added to adjust pH (4.0-7.5). The solution has a tonicity of 1000 mOsm/kg; PRESERVATIVE: benzalkonium chloride 0.01%.

12 CLINICAL PHARMACOLOGY

12.1 Mechanism of Action

Phenylephrine is an alpha-1 adrenergic receptor agonist used for dilation of the pupil due to its vasoconstrictor and mydriatic action. Phenylephrine possesses predominantly α-adrenergic effects. In the eye, phenylephrine acts locally as a potent vasoconstrictor and mydriatic, by constricting ophthalmic blood vessels and the radial muscle of the iris.

12.2 Pharmacodynamics

Maximal mydriasis occurs in 20-90 minutes with recovery after 3 to 8 hours.

Systemic absorption of sufficient quantities of phenylephrine may lead to systemic α-adrenergic effects, such as rise in blood pressure which may be accompanied by a reflex atropine-sensitive bradycardia.

12.3 Pharmacokinetics

The systemic exposure following topical administration of phenylephrine hydrochloride ophthalmic solution has not been studied. A higher systemic absorption is expected for the 10% solution and when the corneal barrier function has been compromised.

14 CLINICAL STUDIES

Pupillary dilation following topical administration of phenylephrine hydrochloride ophthalmic solution has been demonstrated in controlled clinical studies in adults and pediatric patients with different levels of iris pigmentation. Pupil movement is generally seen within 15 minutes, maximal mydriasis between 20 to 90 minutes and recovery after 3 to 8 hours. Darker irides tend to dilate slower than lighter irides.

16 HOW SUPPLIED/STORAGE AND HANDLING

Phenylephrine Hydrochloride Ophthalmic Solution, USP 2.5% is supplied as a sterile, aqueous, topical ophthalmic solution with a fill volume of 10 mL in a 10 mL opaque, white low density polyethylene (LDPE) bottle with a linear low density polyethylene (LLDPE) dropper tip and red cap (NDC 42702-102-10), and a fill volume of 15mL in a 15mL opaque, white LDPE bottle with an LLDPE dropper tip and red cap (NDC 42702-102-15).

Phenylephrine HCl Ophthalmic Solution, USP 10% is supplied as a sterile, aqueous, topical ophthalmic solution supplied with a fill volume of 5 mL in a 10 mL opaque, white LDPE bottle with an LLDPE dropper tip and red cap (NDC 42702-103-05).

Storage and Handling:

Store at 2°C to 25°C (36°F to 77°F).

Keep container tightly closed. Do not use if solution is brown or contains a precipitate.

After opening, Phenylephrine Hydrochloride Ophthalmic Solution, USP can be used until the expiration date on the bottle.

17 PATIENT COUNSELING INFORMATION

Advise patients not to touch the dropper tip to any surface as this may contaminate the solution. Inform patients they may experience sensitivity to light and should protect their eyes in bright illumination while their pupils are dilated.

Distributed by:
Paragon BioTeck, Inc.
Bridgewater, NJ 08807 USA

© 2023 Bausch & Lomb Incorporated or its affiliates

9792900

PACKAGE LABEL

NDC 42702-102-10

Paragon
BioTeck, In c.

Phenylephrine
Hydrochloride
Ophthalmic
Solution, USP 2.5%

FOR TOPICAL
OPHTHALMIC USE.
NOT FOR INJECTION

Rx only

10 mL

9792700

Package/Label Display Panel

NDC 42702-103-05

Paragon
BioTeck, Inc.

Phenylephrine
Hydrochloride
Ophthalmic
Solution, USP 10%

FOR TOPICAL
OPHTHALMIC USE.
NOT FOR INJECTION.

Rx Only

5 mL